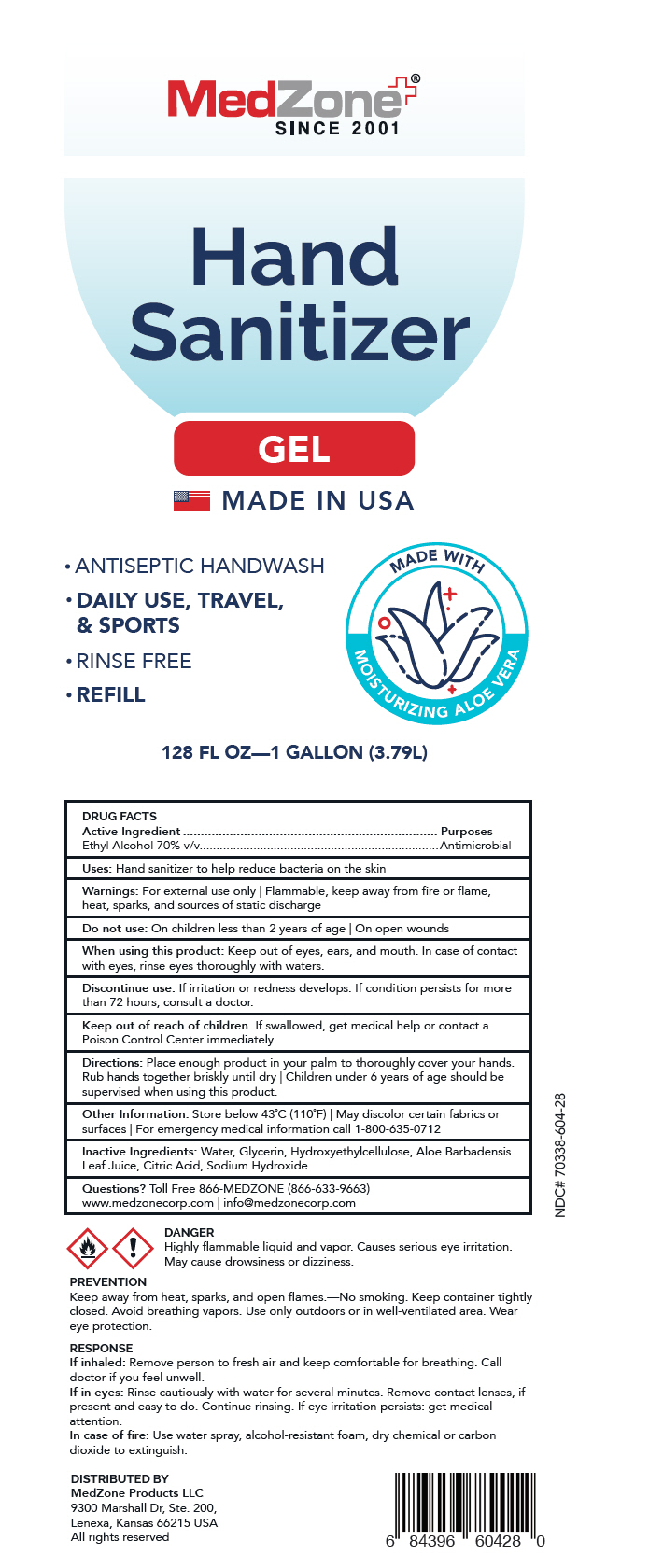 DRUG LABEL: Hand Sanitizer with aloe vera
NDC: 70338-610 | Form: GEL
Manufacturer: MedZone Products, LLC
Category: otc | Type: HUMAN OTC DRUG LABEL
Date: 20200824

ACTIVE INGREDIENTS: Alcohol 70 mL/100 mL
INACTIVE INGREDIENTS: WATER; Glycerin; HYDROXYETHYL CELLULOSE, UNSPECIFIED; ALOE VERA LEAF; CITRIC ACID MONOHYDRATE; Sodium Hydroxide

Hand Sanitizer with aloe vera

DRUG FACTS

Active Ingredient

Ethyl Alcohol 70% v/v

Purposes

Antimicrobial

Uses

Hand sanitizer to help reduce bacteria on the skin

Warnings

For external use only | Flammable, keep away from fire or flame, heat, sparks, and sources of static discharge

Do not use

On children less than 2 years of age | On open wounds

When using this product

Keep out of eyes, ears, and mouth. In case of contact with eyes, rinse eyes thoroughly with waters.

Discontinue use

If irritation or redness develops. If condition persists for more than 72 hours, consult a doctor.

Keep out of reach of children. If swallowed, get medical help or contact a Poison Control Center immediately.

Directions

Place enough product in your palm to thoroughly cover your hands. Rub hands together briskly until dry | Children under 6 years of age should be supervised when using this product.

Other Information

Store below 43˚C (110˚F) | May discolor certain fabrics or surfaces | For emergency medical information call 1-800-635-0712

Inactive Ingredients

Water, Glycerin, Hydroxyethylcellulose, Aloe Barbadensis Leaf Juice, Citric Acid, Sodium Hydroxide

Questions?

Toll Free 866-MEDZONE (866-633-9663)

www.medzonecorp.com | info@medzonecorp.com

DISTRIBUTED BY
MedZone Products LLC
9300 Marshall Dr, Ste. 200,
Lenexa, Kansas 66215 USA

PRINCIPAL DISPLAY PANEL - 3.79 L Bottle Label

MedZone®
SINCE 2001

Hand
Sanitizer

GEL

MADE IN USA

- ANTISEPTIC HANDWASH
- DAILY USE, TRAVEL,
  & SPORTS
- RINSE FREE
- REFILL

MADE WITH
MOISTURIZING ALOE VERA

128 FL OZ—1 GALLON (3.79L)